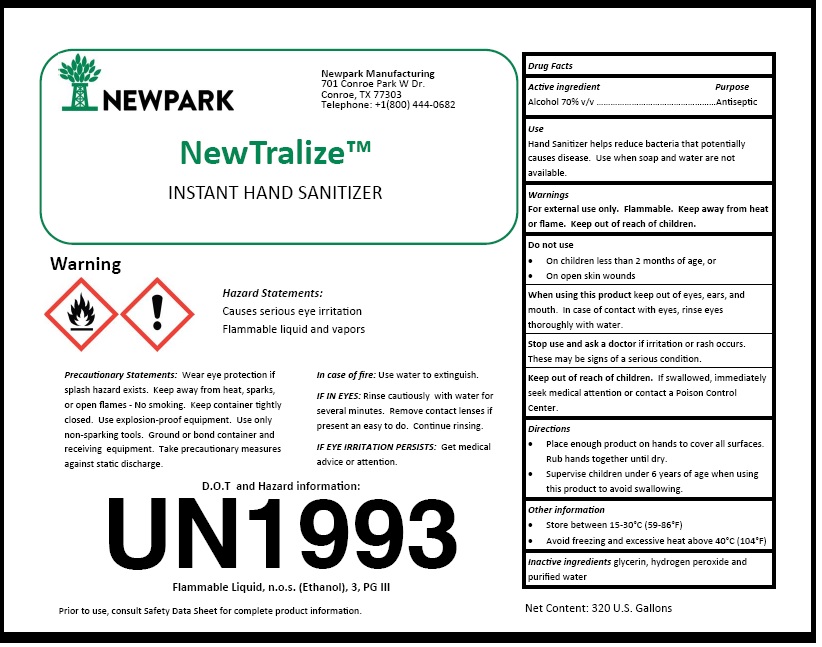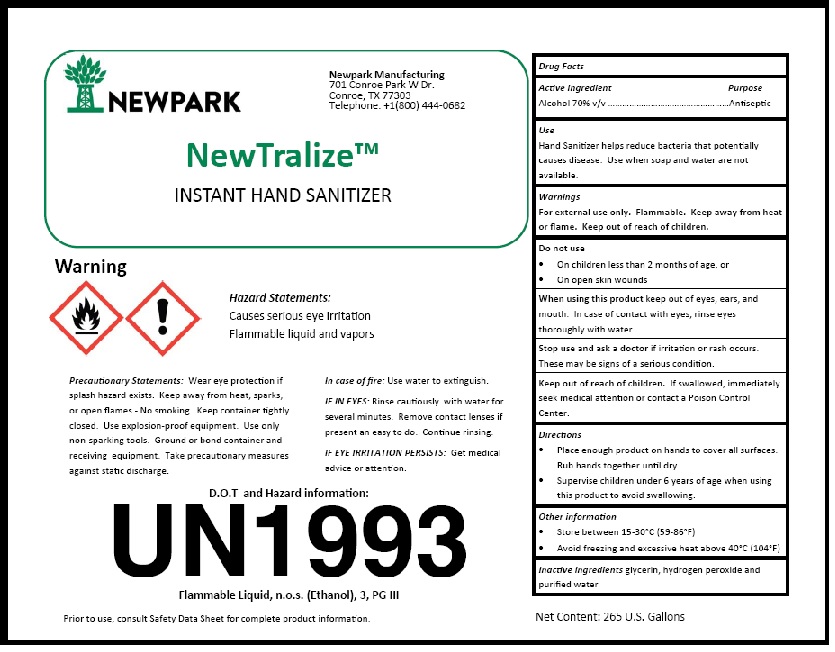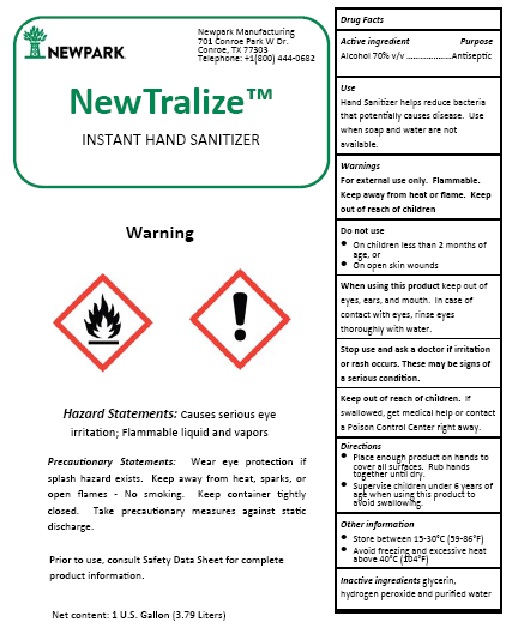 DRUG LABEL: NewTralize
NDC: 75519-001 | Form: LIQUID
Manufacturer: Newpark Industrial Blending Solutions LLC
Category: otc | Type: HUMAN OTC DRUG LABEL
Date: 20211118

ACTIVE INGREDIENTS: ALCOHOL 70 L/100 L
INACTIVE INGREDIENTS: GLYCERIN; HYDROGEN PEROXIDE; WATER

NewTralize™ Instant Hand Sanitizer

Drug Facts

Active Ingredient(s)

Alcohol 70% v/v

Purpose
Antiseptic

Use
Hand Santtizer helps reduce bacteria that potentially
causes disease. Use when soap and water are not
available.

Warnings
For external use only. Flammable. Keep away from heat
or flame. Keep out of reach of children.

Do not use

- On children less than 2 months of age, or
- On open skin wounds

When using this product keep out of eyes, ears, and
mouth. In case of contact with eyes, rinse eyes
thoroughly with water.

Stop use and ask a doctor if irritation or rash occurs.
These may be signs of a serious condi􀆟on.

Keep out of reach of children. If swallowed, immediately
seek medical attention or contact a Poison Control
Center.

Directions

- Place enough product on hands to cover all surfaces.
- Rub hands together until dry.
- Supervise children under 6 years of age when usingthis product to avoid swallowing.

Other information

- Store between 15-30°C (59-86°F)
- Avoid freezing and excessive heat above 40°C (104°F)

Inactive ingredients glycerin, hydrogen peroxide and
purified water

Package Label - Principal Display Panel

NEWPARK

Newpark Manufacturing
701 Conroe Park W Dr.
Conroe, TX 77303
Telephone: +1(800) 444-0682

NewTralize™
INSTANT HAND SANITIZER

Warning

Hazard Statements:

Causes serious eye irritation
Flammable liquid and vapors

Precautionary Statements: Wear eye protection if
splash hazard exists. Keep away from heat, sparks,
or open flames - No smoking. Keep container tightly
closed. Use explosion-proof equipment. Use only
non-sparking tools. Ground or bond container and
receiving equipment. Take precautionary measures
against static discharge.

In case of fire: Use water to extinguish.

IF IN EYES: Rinse cautiously with water for
several minutes. Remove contact lenses if
present an easy to do. Continue rinsing.

IF EYE IRRITATION PERSISTS: Get medical
advice or attention.

D.O.T and Hazard information:

UN1993

Flammable Liquid, n.o.s. (Ethanol), 3, PG III
Prior to use, consult Safety Data Sheet for complete product information.

Net Content: 320 U.S. Gallons

res